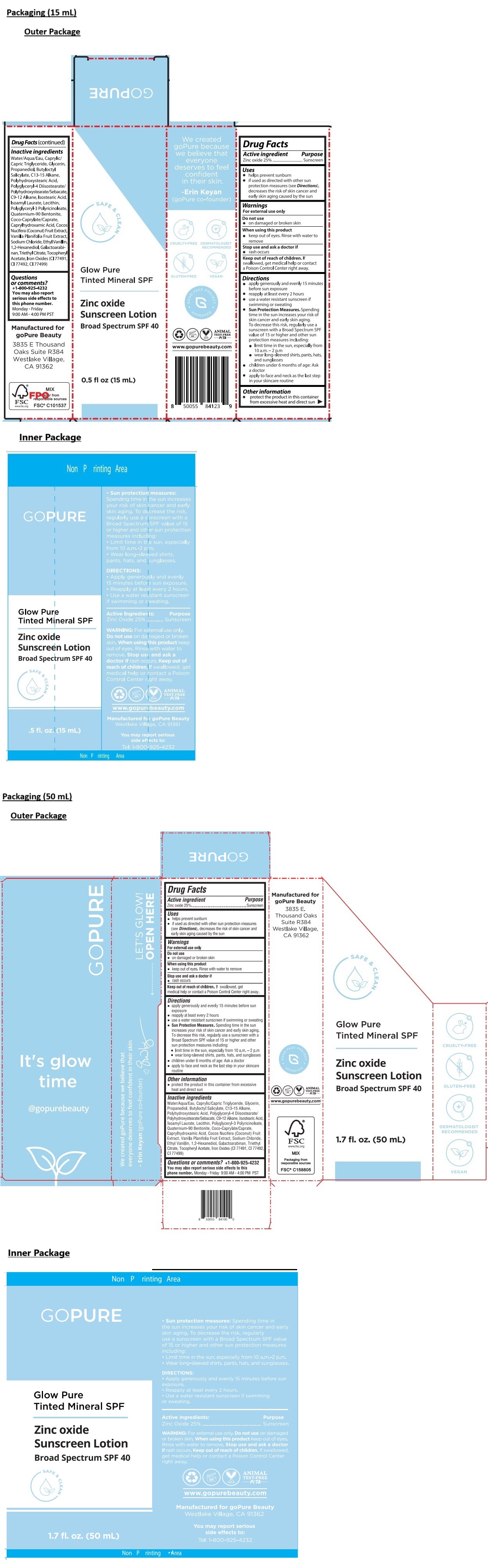 DRUG LABEL: goPure Sunscreen
NDC: 83448-025 | Form: LOTION
Manufacturer: Natural Lifestyle Brands, LLC dba GoPure beauty
Category: otc | Type: HUMAN OTC DRUG LABEL
Date: 20251027

ACTIVE INGREDIENTS: ZINC OXIDE 25 g/100 mL
INACTIVE INGREDIENTS: WATER; MEDIUM-CHAIN TRIGLYCERIDES; GLYCERIN; PROPANEDIOL; BUTYLOCTYL SALICYLATE; C13-15 ALKANE; POLYHYDROXYSTEARIC ACID (2300 MW); POLYGLYCERYL-4 DIISOSTEARATE/POLYHYDROXYSTEARATE/SEBACATE; C9-12 ALKANE; ISOSTEARIC ACID; ISOAMYL LAURATE; LECITHIN, SUNFLOWER; POLYGLYCERYL-3 PENTARICINOLEATE; QUATERNIUM-90 BENTONITE; COCOYL CAPRYLOCAPRATE; CAPRYLHYDROXAMIC ACID; COCONUT; VANILLA BEAN; SODIUM CHLORIDE; ETHYL VANILLIN; 1,2-HEXANEDIOL; GALACTOARABINAN; TRIETHYL CITRATE; .ALPHA.-TOCOPHEROL ACETATE; FERRIC OXIDE YELLOW; FERRIC OXIDE RED; FERROSOFERRIC OXIDE

Zinc oxide Sunscreen Lotion

Active ingredient

Zinc oxide 25%

Purpose

Sunscreen

Uses

• helps prevent sunburn
• if used as directed with other sun protection measures (see Directions), decreases the risk of skin cancer and early skin aging caused by the sun

Warnings

For external use only

Do not use
• on damaged or broken skin

When using this product
• keep out of eyes. Rinse with water to remove

Stop use and ask a doctor if
• rash occurs

Keep out of reach of children. If swallowed, get medical help or contact a Poison Control Center right away.

Directions

• apply generously and evenly 15 minutes before sun exposure
• reapply at least every 2 hours
• use a water resistant sunscreen if swimming or sweating
• Sun Protection Measures. Spending time in the sun increases your risk of skin cancer and early skin aging. To decrease this risk, regularly use a sunscreen with a Broad Spectrum SPF value of 15 or higher and other sun protection measures including:
• limit time in the sun, especially from 10 a.m. – 2 p.m
• wear long-sleeved shirts, pants, hats, and sunglasses
• children under 6 months of age: Ask a doctor
• apply to face and neck as the last step in your skincare routine

Other information

• protect the product in this container from excessive heat and direct sun

Inactive ingredients

Water/Aqua/Eau, Caprylic/Capric Triglyceride, Glycerin, Propanediol, Butyloctyl Salicylate, C13-15 Alkane, Polyhydroxystearic Acid, Polyglyceryl-4 Diisostearate/Polyhydroxystearate/Sebacate, C9-12 Alkane, Isostearic Acid, Isoamyl Laurate, Lecithin, Polyglyceryl-3 Polyricinoleate, Quaternium-90 Bentonite, Coco-Caprylate/Caprate, Caprylhydroxamic Acid, Cocos Nucifera (Coconut) Fruit Extract, Vanilla Planifolia Fruit Extract, Sodium Chloride, Ethyl Vanillin, 1,2-Hexanediol, Galactoarabinan, Triethyl Citrate, Tocopheryl Acetate, Iron Oxides (CI 77491, CI 77492, CI 77499)

Questions or comments?

+1-800-925-4232

You may also report serious side effects to this phone number. Monday - Friday 9:00 AM - 4:00 PM PST

SAFE & CLEAN

Glow Pure Tinted Mineral SPF

Broad Spectrum SPF 40

CRUELTY-FREE

GLUTEN-FREE

DERMATOLOGIST RECOMMENDED

VEGAN

It's glow time

@gopurebeauty

We created goPure because we believe that everyone deserves to feel confident in their skin -Erin Keyan (goPure co-founder)

LET'S GLOW!

Manufactured for
goPure Beauty
3835 E.
Thousand Oaks
Suite R384
Westlake Village,
CA 91362

GOOD FACE PROJECT APPROVED

ANIMAL TEST-FREE
PeTA

www.gopurebeauty.com

FSC® C158805

FPO